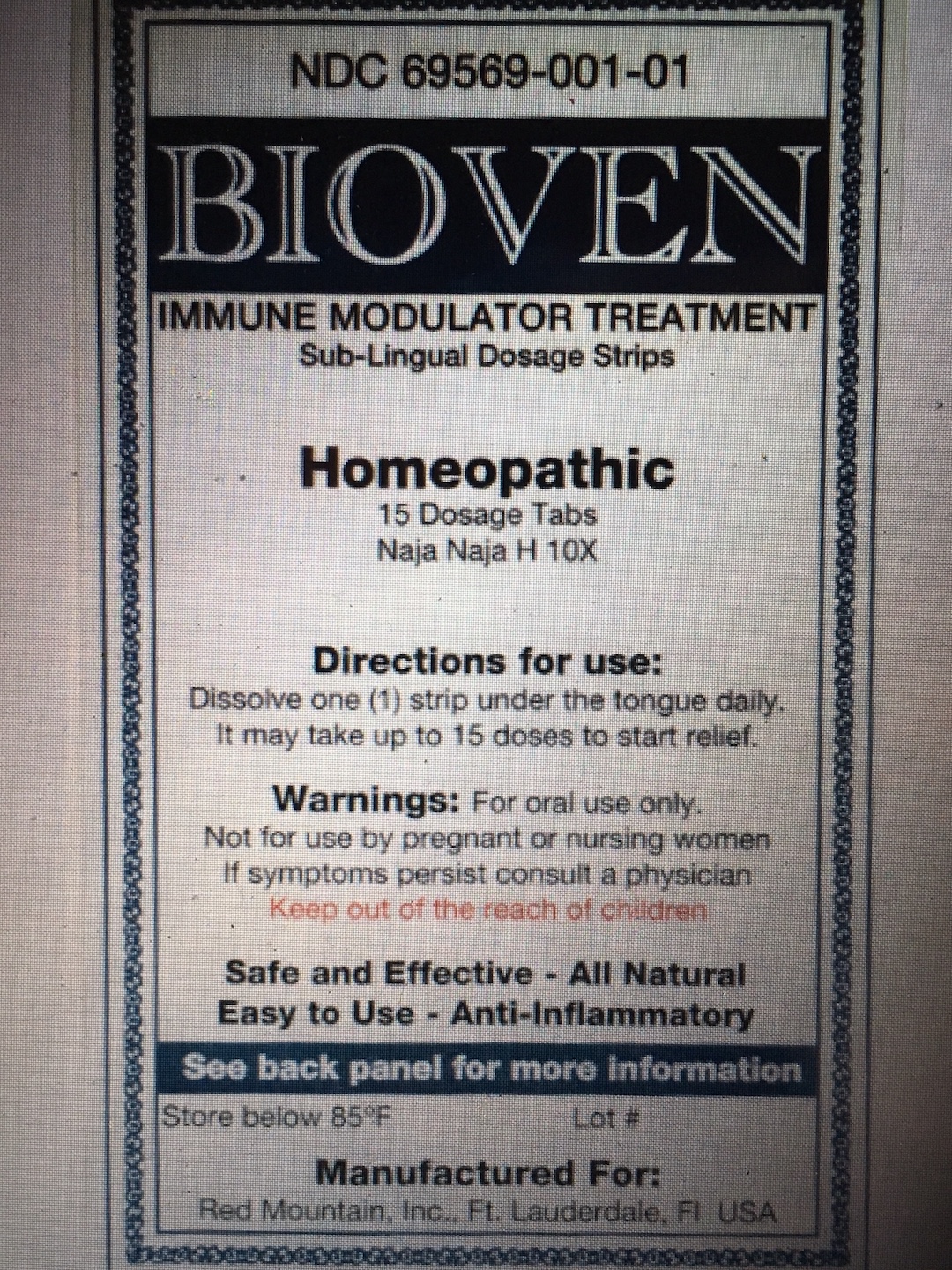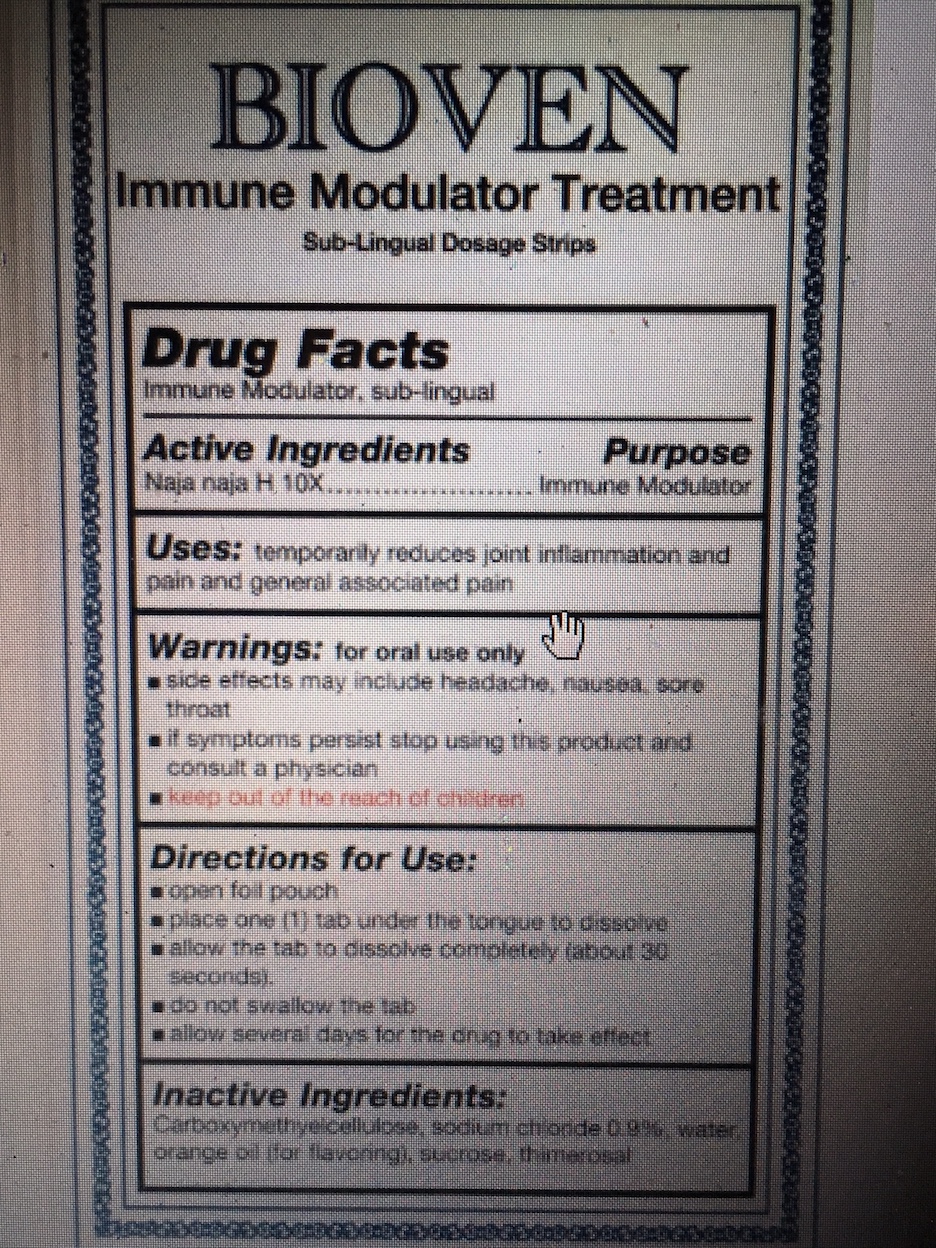 DRUG LABEL: Bioven
NDC: 69569-001 | Form: STRIP
Manufacturer: Red Mountain, Inc.
Category: homeopathic | Type: HUMAN OTC DRUG LABEL
Date: 20190520

ACTIVE INGREDIENTS: NAJA NAJA VENOM 10 [hp_X]/1 1
INACTIVE INGREDIENTS: CARBOXYMETHYLCELLULOSE; SODIUM CHLORIDE; WATER; SUCROSE; THIMEROSAL; ORANGE OIL

Bioven

WARNINGS

For oral use only

If symptoms persist stop using this product and consult a physician

Side effects may include headache, nausea, sore throat

Directions for use

Dissolve one (1) strip under the tongue daily. It may take up to 15 doses to start relief.

Keep out of reach of children

ACTIVE INGREDIENT

Naja Naja H 10X

INACTIVE INGREDIENT

Carboxymethyelcellulose, sodium chloride 0.9%, water, natural orange flavorings, sucrose , thimerosol

PURPOSE

Immune Modulator

PREGNANCY OR BREAST FEEDING

Not for use by pregnant or nursing women

Uses

Promotes good health by helping the body support defficiencies in the immune system.